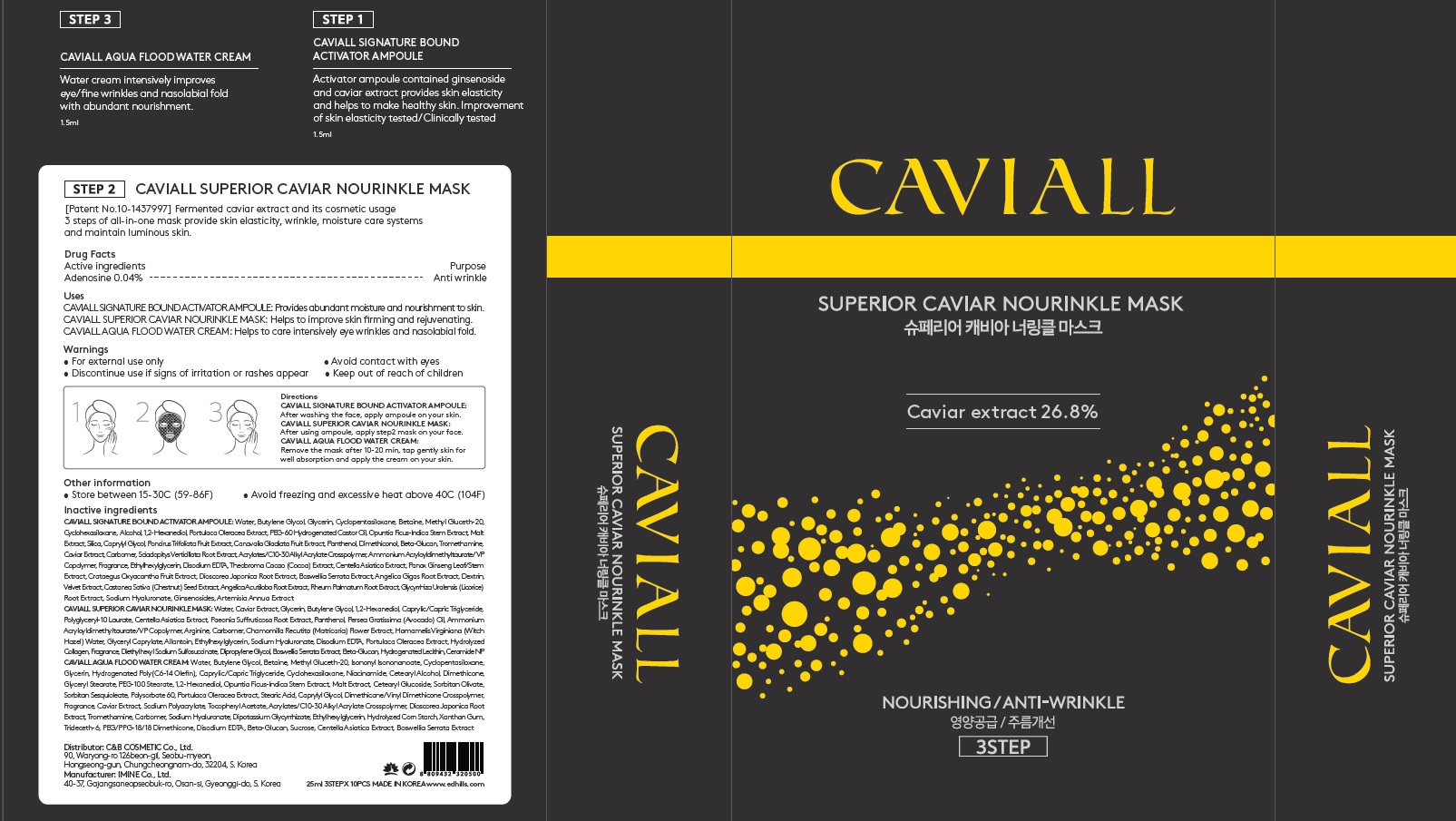 DRUG LABEL: CAVIALL Superior Caviar Nourinkle Mask SET
NDC: 60611-0120 | Form: KIT | Route: TOPICAL
Manufacturer: C&BCOSMETIC Co., Ltd.
Category: otc | Type: HUMAN OTC DRUG LABEL
Date: 20210127

ACTIVE INGREDIENTS: Adenosine 0.01 g/25 mL; Adenosine 0.0006 g/1.5 mL; Adenosine 0.0006 g/1.5 mL
INACTIVE INGREDIENTS: WATER; CAVIAR, UNSPECIFIED; WATER; BUTYLENE GLYCOL; WATER; BUTYLENE GLYCOL

ACTIVE INGREDIENT

Adenosine 0.04%

INACTIVE INGREDIENTS

[CAVIALL Signature Bound Activator Ampoule]

Water, Butylene Glycol, Glycerin, Cyclopentasiloxane, Betaine, Methyl Gluceth-20, Cyclohexasiloxane, Alcohol, 1,2-Hexanediol, Portulaca Oleracea Extract, PEG-60 Hydrogenated Castor Oil, Opuntia Ficus-Indica Stem Extract, Malt Extract, Silica, Caprylyl Glycol, Poncirus Trifoliata Fruit Extract, Canavalia Gladiata Fruit Extract, Panthenol, Dimethiconol, Beta-Glucan, Tromethamine, Caviar Extract, Carbomer, Sciadopitys Verticillata Root Extract, Acrylates/C10-30 Alkyl Acrylate Crosspolymer, Ammonium Acryloyldimethyltaurate/VP Copolymer, Fragrance, Ethylhexylglycerin, Disodium EDTA, Theobroma Cacao (Cocoa) Extract, Centella Asiatica Extract, Panax Ginseng Leaf/Stem Extract, Crataegus Oxyacantha Fruit Extract, Dioscorea Japonica Root Extract, Boswellia Serrata Extract, Angelica Gigas Root Extract, Dextrin, Velvet Extract, Castanea Sativa (Chestnut) Seed Extract, Angelica Acutiloba Root Extract, Rheum Palmatum Root Extract, Glycyrrhiza Uralensis (Licorice) Root Extract, Sodium Hyaluronate, Ginsenosides, Artemisia Annua Extract

[CAVIALL Superior Caviar Nourinkle Mask]

Water, Caviar Extract, Glycerin, Butylene Glycol, 1,2-Hexanediol, Caprylic/Capric Triglyceride, Polyglyceryl-10 Laurate, Centella Asiatica Extract, Paeonia Suffruticosa Root Extract, Panthenol, Persea Gratissima (Avocado) Oil, Ammonium Acryloyldimethyltaurate/VP Copolymer, Arginine, Carbomer, Chamomilla Recutita (Matricaria) Flower Extract, Hamamelis Virginiana (Witch Hazel) Water, Glyceryl Caprylate, Allantoin, Ethylhexylglycerin, Sodium Hyaluronate, Disodium EDTA, Portulaca Oleracea Extract, Hydrolyzed Collagen, Fragrance, Diethylhexyl Sodium Sulfosuccinate, Dipropylene Glycol, Boswellia Serrata Extract, Beta-Glucan, Hydrogenated Lecithin, Ceramide NP

[CAVIALL Aqua Flood Water Cream]

Water, Butylene Glycol, Betaine, Methyl Gluceth-20, Isononyl Isononanoate, Cyclopentasiloxane, Glycerin, Hydrogenated Poly(C6-14 Olefin), Caprylic/Capric Triglyceride, Cyclohexasiloxane, Niacinamide, Cetearyl Alcohol, Dimethicone, Glyceryl Stearate, PEG-100 Stearate, 1,2-Hexanediol, Opuntia Ficus-Indica Stem Extract, Malt Extract, Cetearyl Glucoside, Sorbitan Olivate, Sorbitan Sesquioleate, Polysorbate 60, Portulaca Oleracea Extract, Stearic Acid, Caprylyl Glycol, Dimethicone/Vinyl Dimethicone Crosspolymer, Fragrance, Caviar Extract, Sodium Polyacrylate, Tocopheryl Acetate, Acrylates/C10-30 Alkyl Acrylate Crosspolymer, Dioscorea Japonica Root Extract, Tromethamine, Carbomer, Sodium Hyaluronate, Dipotassium Glycyrrhizate, Ethylhexylglycerin, Hydrolyzed Corn Starch, Xanthan Gum, Trideceth-6, PEG/PPG-18/18 Dimethicone, Disodium EDTA, Beta-Glucan, Sucrose, Centella Asiatica Extract, Boswellia Serrata Extract

PURPOSE

Anti Wrinkle

WARNINGS

For external use only
Avoid contact with eyes.
Discontinue use if signs of irritation or rashes appear.
Keep out of reach of children

KEEP OUT OF REACH OF CHILDREN

Uses

[CAVIALL Signature Bound Activator Ampoule]

Provides abundant moisture and nourishment to skin.

[CAVIALL Superior Caviar Nourinkle Mask]

Helps to improve skin firming and rejuvenating.

[CAVIALL Aqua Flood Water Cream]

Helps to care intensively eye wrinkles and nasolabial fold.

Directions

[CAVIALL Signature Bound Activator Ampoule]
After washing the face, apply ampoule on your skin

[CAVIALL Superior Caviar Nourinkle Mask]
After using ampoule, apply step2 mask on your face.

[CAVIALL Aqua Flood Water Cream]

Remove the mask after 10-20 min, tap gently skin for well absorption and apply the cream on your skin.

Other information

• Store between 15-30C (59-86F)
• Avoid freezing and excessive heat above 40C (104F)